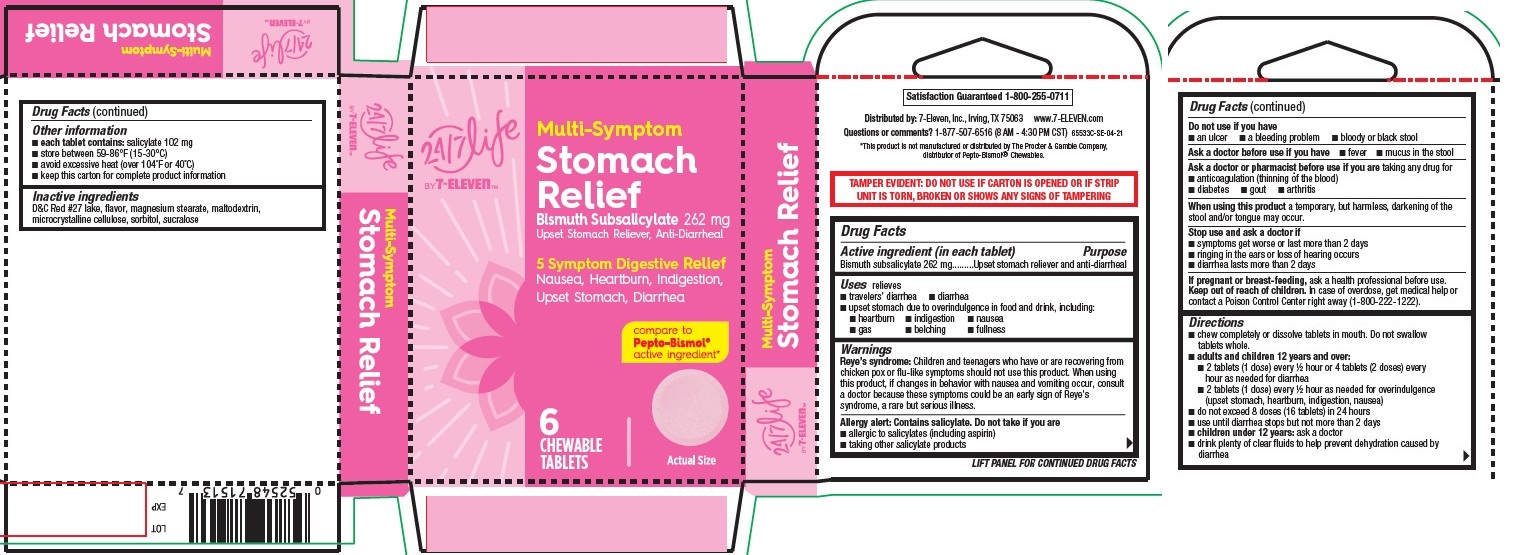 DRUG LABEL: Stomach Relief, 24-7 Life by 7-Eleven
NDC: 66715-8153 | Form: TABLET, CHEWABLE
Manufacturer: Lil' Drug Store products, Inc.
Category: otc | Type: HUMAN OTC DRUG LABEL
Date: 20251212

ACTIVE INGREDIENTS: BISMUTH SUBSALICYLATE 262 mg/1 1
INACTIVE INGREDIENTS: SUCRALOSE; MAGNESIUM STEARATE; MICROCRYSTALLINE CELLULOSE; MALTODEXTRIN; D&C RED NO. 27; SORBITOL

Stomach Relief, 24/7 Life by 7-ElevenTM

Drug Facts

Active ingredient

Active ingredient (in each tablet)

Bismuth subsalicylate 262 mg

Purpose

Upset stomach reliever and anti-diarrheal

Uses

relieves

- travelers’ diarrhea
- diarrhea
- upset stomach due to overindulgence in food and drink, including:
- heartburn
- indigestion
- nausea
- gas
- belching
- fullness

Warnings

Reye’s syndrome: Children and teenagers who have or are recovering from chicken pox or flu-like symptoms should not use this product. When using this product, if changes in behavior with nausea and vomiting occur, consult a doctor because these symptoms could be an early sign of Reye's syndrome, a rare but serious illness.

Allergy alert

Allergy alert: Contains salicylate. Do not take if you are

- allergic to salicylates (including aspirin)
- taking other salicylate products

Do not use if you have

- an ulcer
- a bleeding problem
- bloody or black stool

Ask a doctor before use if you have

- fever
- mucus in the stool

Ask a doctor or pharmacist before use if you are taking any drug for

- anticoagulation (thinning of the blood)
- diabetes
- gout
- arthritis

When using this product a temporary, but harmless, darkening of the stool and/or tongue may occur.

Stop use and ask a doctor if

- symptoms get worse or last more than 2 days
- ringing in the ears or loss of hearing occurs
- diarrhea lasts more than 2 days

If pregnant or breast-feeding, ask a health professional before use.

Keep out of reach of children. In case of overdose, get medical help or contact a Poison Control Center right away (1-800-222-1222).

Directions

- chew completely or dissolve tablets in mouth. Do not swallow tablets whole.
- adults and children 12 years and over:
- 2 tablets (1 dose) every ½ hour or 4 tablets (2 doses) every hour as needed for diarrhea
- 2 tablets (1 dose) every ½ hour as needed for overindulgence (upset stomach, heartburn, indigestion, nausea)
- do not exceed 8 doses (16 tablets) in 24 hours
- use until diarrhea stops but not more than 2 days
- children under 12 years: ask a doctor
- drink plenty of clear fluids to help prevent dehydration caused by diarrhea

Other information

- each tablet contains: salicylate 102 mg
- store between 59-86°F (15-30°C)
- avoid excessive heat (over 104°F or 40°C)
- keep this carton for complete product information

Inactive ingredients

D&C Red #27 lake, flavor, magnesium stearate, maltodextrin, microcrystalline cellulose, sorbitol, sucralose

Stomach Relief, 24/7 Life by 7-ElevenTM

[ 24/7 Life by 7-ElevenTM logo]

Multi-Symptom
Stomach
Relief

Bismuth Subsalicylate 262 mg
Upset Stomach Reliever, Anti-Diarrheal

5 Symptom Digestive Relief
Nausea, Heartburn, Indigestion,
Upset Stomach, Diarrhea

compare to

Pepto-Bismol®

active ingredient

6

CHEWABLE

TABLETS

[tablet image]

Actual Size